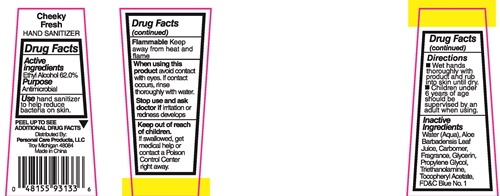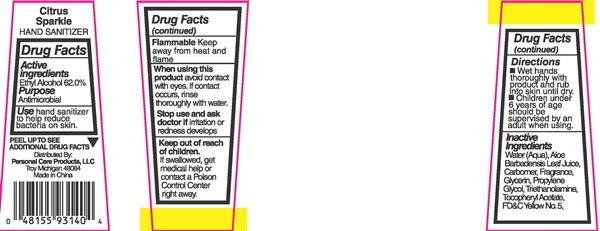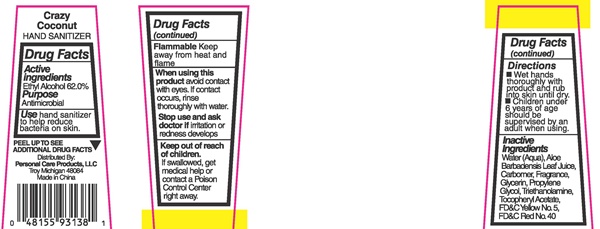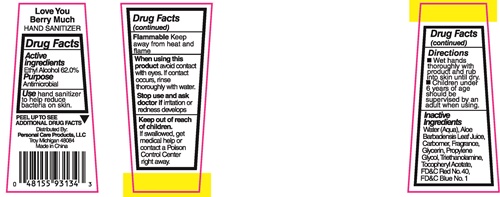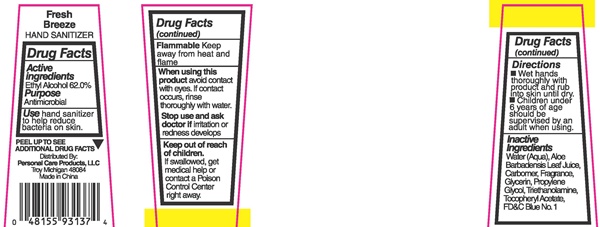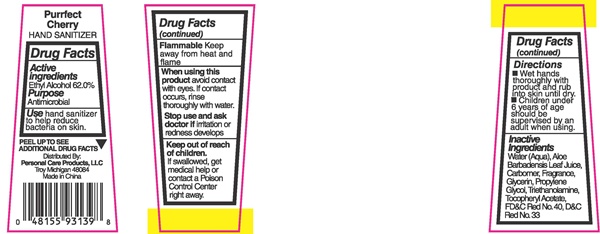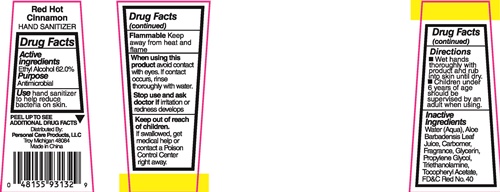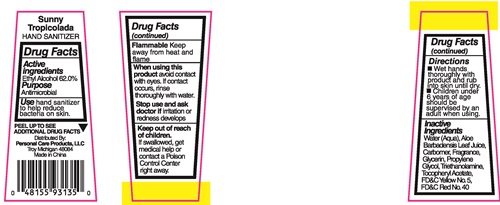 DRUG LABEL: Red Hot Cinnamon
NDC: 29500-9132 | Form: LIQUID
Manufacturer: Personal Care Products LLC
Category: otc | Type: HUMAN OTC DRUG LABEL
Date: 20170117

ACTIVE INGREDIENTS: ALCOHOL 26.36 g/44 mL
INACTIVE INGREDIENTS: WATER; ALOE VERA LEAF; CARBOXYPOLYMETHYLENE; GLYCERIN; PROPYLENE GLYCOL; TROLAMINE; .ALPHA.-TOCOPHEROL ACETATE; FD&C RED NO. 40

Red Hot Cinnamon - 9132
Cheeky Fresh - 9133
Love You Berry Much - 9134
Sunny Tropicolada - 9135
Fresh Breeze - 9137
Crazy Coconut - 9138
Purrfect Cherry - 9139
Citrus Sparkle - 9140

Drug Facts Active ingredients

Ethly Alcohol 62.0 %

Purpose

Antimicrobial

Keep out of reach of children.

If swallowed, get medical help or contact a Poison Control Center right away.

Use

hand sanitizer to help reduce bacteria on skin.

Warnings

Flammable

Keep away from heat and flame.

When using this product

avoid contact with eyes. If contact occurs, rinse thoroughly with water.

Stop use and ask as doctor if

irritation or redness develops

Directions

- Wet hands thoroughly with product and rub into skin until dry.

- Children under 6 years of age should be supervised by an adult when using.

Inactive Ingredients

Water (Aqua), Aloe Barbadensis Leaf Juice, Carbomer, Fragrance, Glycerin, Propylene Glycol, Triethanolamine, Tocopheryl Acetate. FD&C Blue No. 1, FD&C Red No. 40, FD&C Yellow No. 5, D&C Red No. 33

Red Hot Cinnamon - 9132 Cheeky Fresh - 9133 Love You Berry Much - 9134 Sunny Tropicolada - 9135 Fresh breeze - 9137 Crazy Coconut - 9138 Purrfect Cherry - 9139 Citrus Sparkle - 9140 product labels

Red Hot Cinnamon

HAND SANITIZER

PEEL UP TO SEE ADDITIONAL DRUG FACTS
Distrubuted By:
Personak Care Products, LLC
Troy Michigan, 48084
Made in China

Cheeky Fresh

HAND SANITIZER

PEEL UP TO SEE ADDITIONAL DRUG FACTS
Distrubuted By:
Personak Care Products, LLC
Troy Michigan, 48084
Made in China

Love You Berry Much

HAND SANITIZER

PEEL UP TO SEE ADDITIONAL DRUG FACTS
Distrubuted By:
Personak Care Products, LLC
Troy Michigan, 48084
Made in China

Sunny Tropicolada

HAND SANITIZER

PEEL UP TO SEE ADDITIONAL DRUG FACTS
Distrubuted By:
Personak Care Products, LLC
Troy Michigan, 48084
Made in China

Fresh Breeze

HAND SANITIZER

PEEL UP TO SEE ADDITIONAL DRUG FACTS
Distrubuted By:
Personak Care Products, LLC
Troy Michigan, 48084
Made in China

Crazy Coconut

HAND SANITIZER

PEEL UP TO SEE ADDITIONAL DRUG FACTS
Distrubuted By:
Personak Care Products, LLC
Troy Michigan, 48084
Made in China

Purrfect Cherry

HAND SANITIZER

PEEL UP TO SEE ADDITIONAL DRUG FACTS
Distrubuted By:
Personak Care Products, LLC
Troy Michigan, 48084
Made in China

Citrus Sparkle

HAND SANITIZER

PEEL UP TO SEE ADDITIONAL DRUG FACTS
Distrubuted By:
Personak Care Products, LLC
Troy Michigan, 48084
Made in China